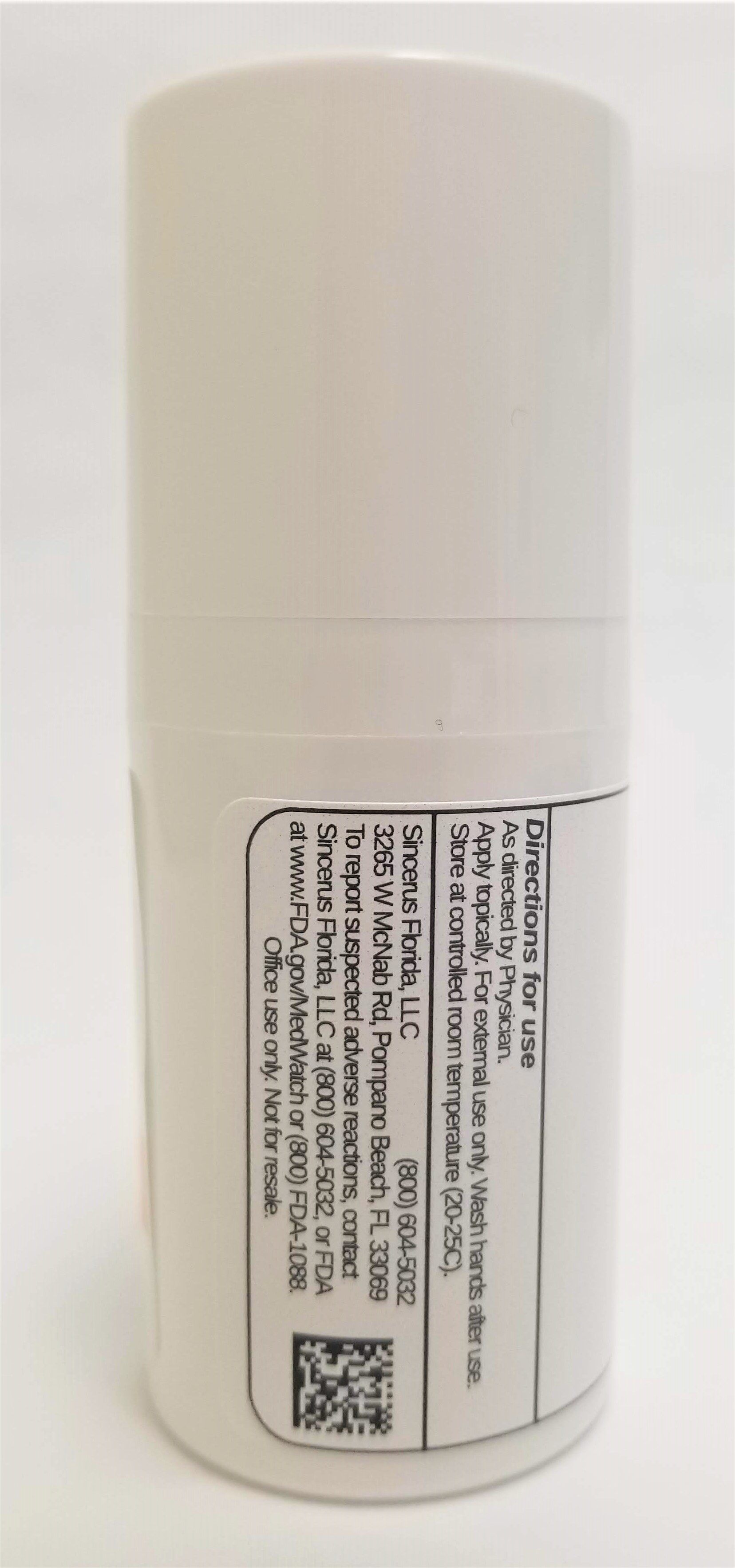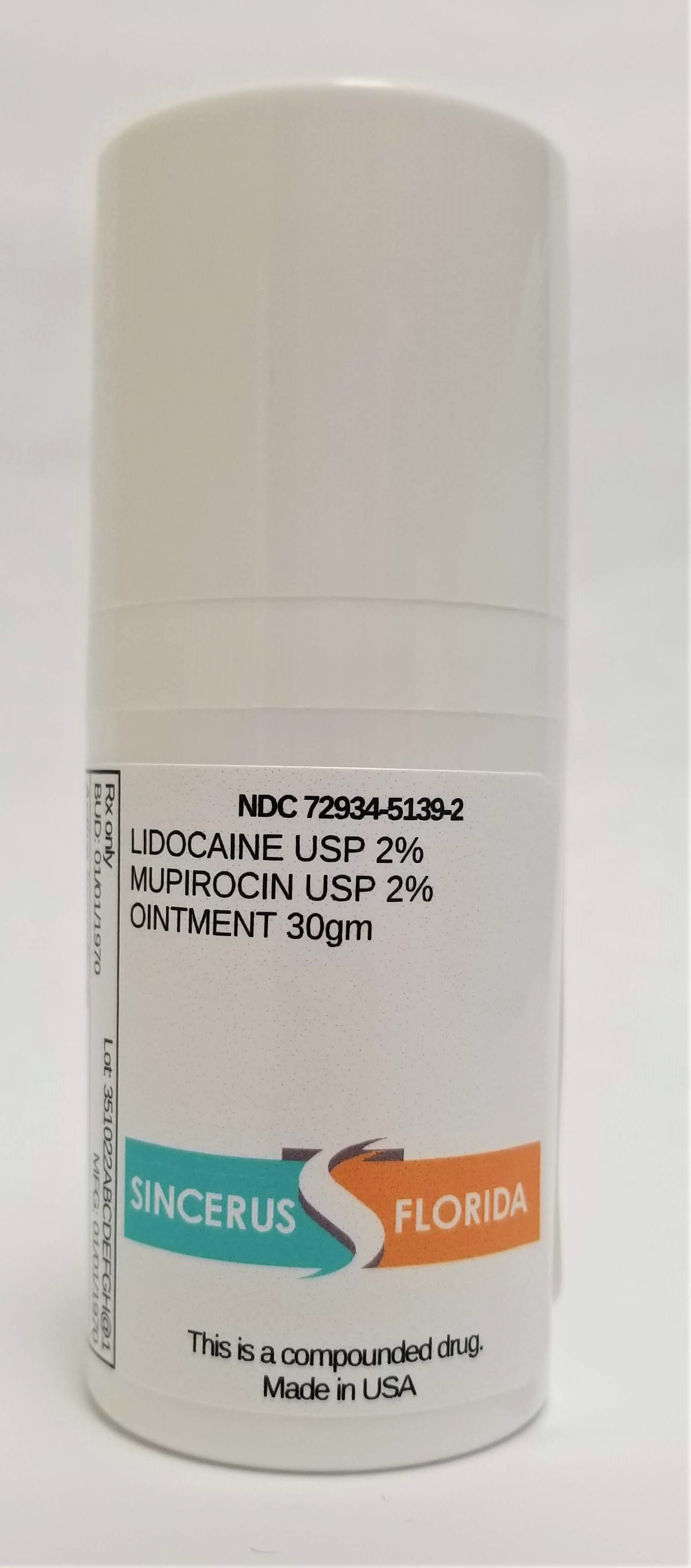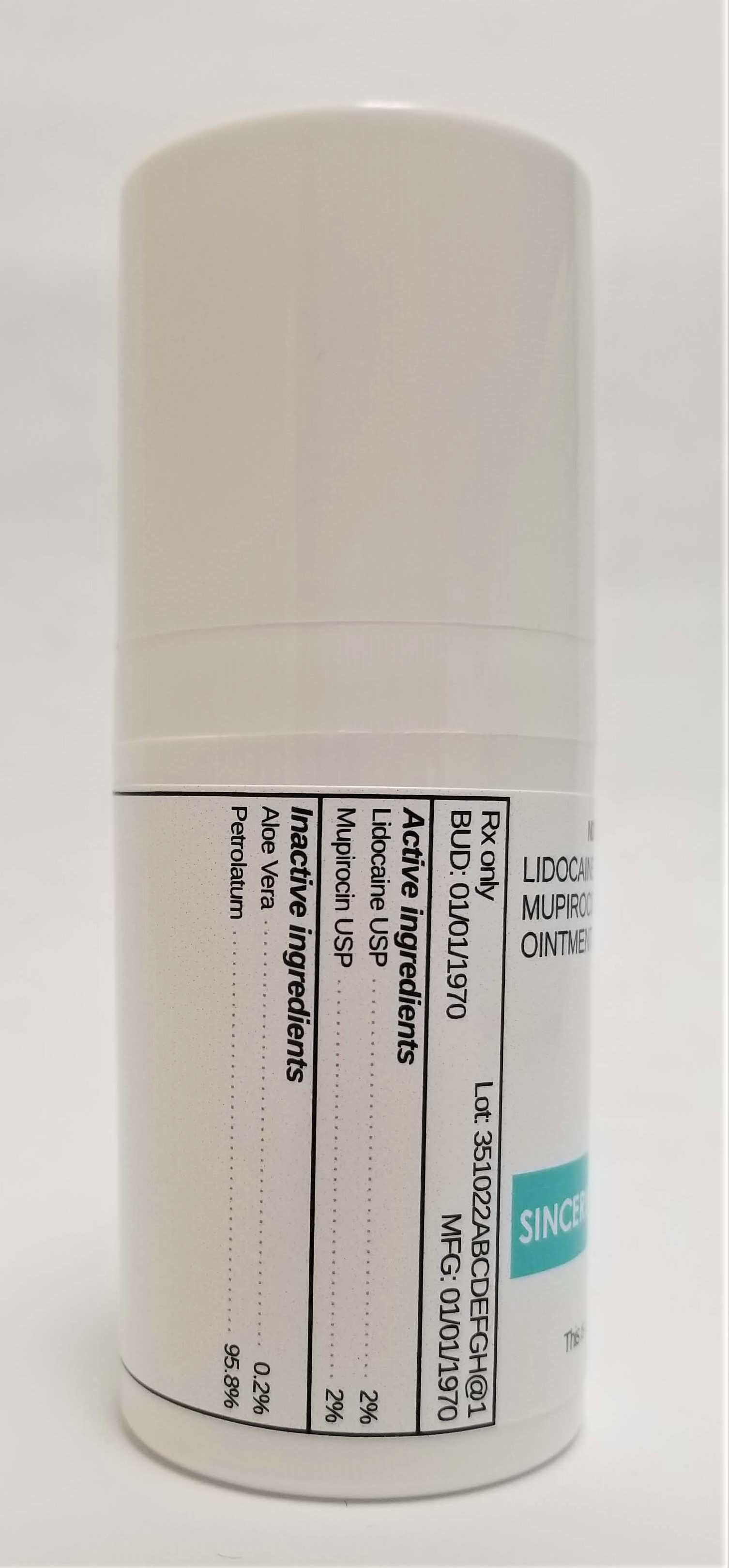 DRUG LABEL: LIDOCAINE 2% / MUPIROCIN 2%
NDC: 72934-5139 | Form: OINTMENT
Manufacturer: Sincerus Florida, LLC
Category: prescription | Type: HUMAN PRESCRIPTION DRUG LABEL
Date: 20190514

ACTIVE INGREDIENTS: MUPIROCIN 2 g/100 g; LIDOCAINE 2 g/100 g

LIDOCAINE 2% / MUPIROCIN 2%